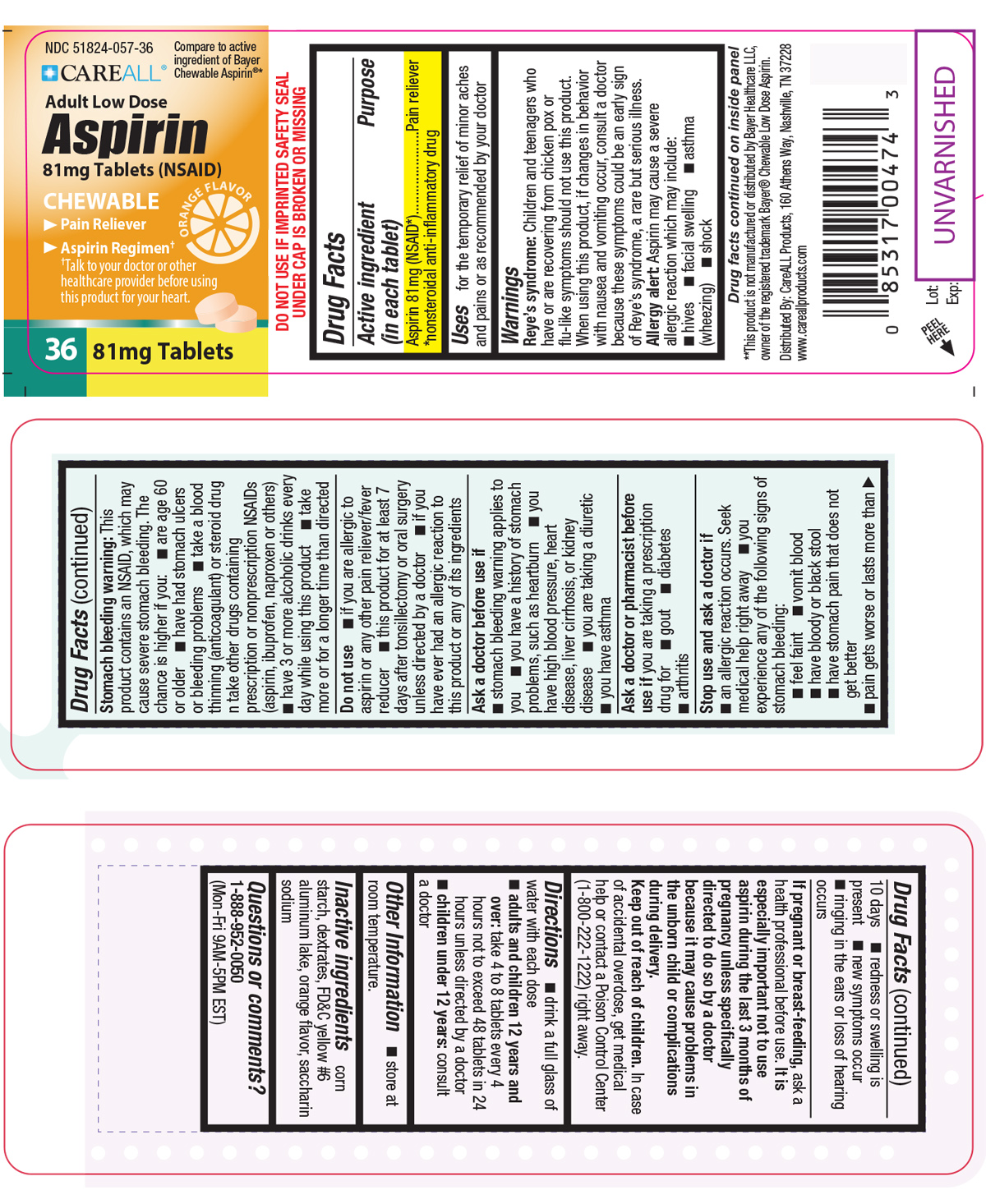 DRUG LABEL: CAREALL Aspirin
NDC: 51824-057 | Form: TABLET, CHEWABLE
Manufacturer: New World Imports, Inc
Category: otc | Type: HUMAN OTC DRUG LABEL
Date: 20251222

ACTIVE INGREDIENTS: ASPIRIN 81 mg/1 1
INACTIVE INGREDIENTS: DEXTRATES; SACCHARIN SODIUM; STARCH, CORN; FD&C YELLOW NO. 6

Drug Facts

Active Ingredient

Aspirin 81 mg (NSAID*)

*nonsteroidal anti-inflammatory drug

Purpose

Pain reliever

Keep out of reach of children.

In case of accidental overdose, get medical help or contact aPoison Control Center (1-800-222-1222) right away

Uses

for the temporary relief of minor aches and paines or as recommended by your doctor

Warnings

Reye's syndrome:Children and teenagers who have or are recovering from chicken pox or flu-like symptoms should not use this product. When using this product, if changes in behavior with nausea and vomiting occur, consult a doctor because these symptoms could be an early sign of Reye's syndrome, a rare but serious illness.

Allergy Alert:Aspirin may cause a severe allergic reaction which may include hives, facial swelling, asthma (wheezing), shock.

Stomach Bleeding Warning:This product contains NSAID, which may cause severe stomach bleeding. The chance is higher if you:

-Have had stomach ulcers or bleeding problems

-Take a blood thinning (anticoagulant) or steroid drug

-Take other drugs containing prescription or nonprescription NSAIDs (aspirin, ibuprofen, naproxen, or others)

-Take more or for a longer time than directed

-Are age 60 or older

-Have 3 or more alcoholic drinks every day while using this product

Do not use:

-if you are allergic to aspirin or other pain relievers / fever reducers

-For at least 7 days after tonsillectomy or oral surgery unless directed by a doctor

-If you have ever had an allergic reaction to this product or any of its ingredients

Ask a doctor before use if:

-Stomach bleeding warning applies to user

-you have a history of stomach problems, such as heartburn

-you have high blood pressure, heart disease, liver cirrhosis, or kidney disease

-you are taking a diuretic

-You have asthma

Ask a doctor of pharmacist before use if youare taking a prescription drug for diabetes, gout, or arthritis.

Stop use and ask a doctor if:

-You experience any of the following signs of stomach bleeding: feel faint, vomit blood, has bloody or black stool, has stomach pain that does not get better

-An allergic reaction occurs. Seek medical help help right away

-New symptoms occur

-Redness or swelling is present

-Pain gets worse or lasts for more than 10 days

-Ringing in the ears or loss of hearing occurs

-You may report side effects to 1-888-952-0050

If pregnant or breast-feeding,ask a health professional before use. It is especially important not to use aspirin during the last 3 months of pregnancy unless specifically directed to do so by a doctor because it may cause problems in unborn child or complications during delivery.

Directions

Drink a full glass of water with each dose.

Adults and children 12 years and over: take 4 to 8 tablets every 4 hours. Not to exceed 48 tablets in 24 hours unless directed by a doctor.

Children under 12:consult a doctor

Inactive Ingredients

corn starch, dextrates, FD C yellow 6 aluminum lake, orange flavor, saccharin sodium